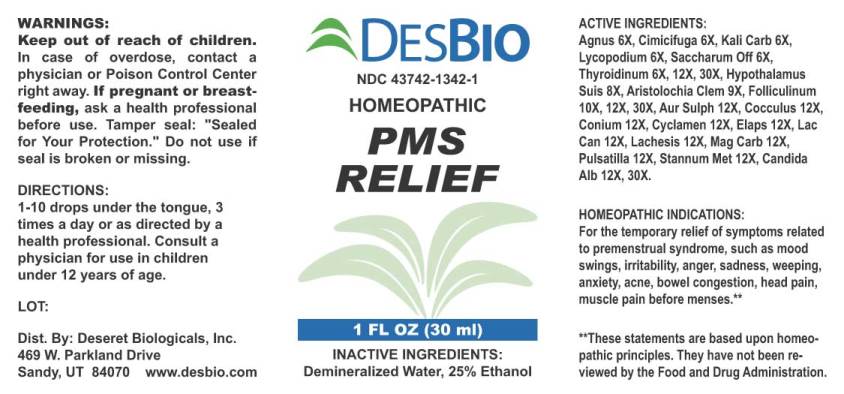 DRUG LABEL: PMS Relief
NDC: 43742-1342 | Form: LIQUID
Manufacturer: Deseret Biologicals, Inc.
Category: homeopathic | Type: HUMAN OTC DRUG LABEL
Date: 20240911

ACTIVE INGREDIENTS: CHASTE TREE FRUIT 6 [hp_X]/1 mL; BLACK COHOSH 6 [hp_X]/1 mL; POTASSIUM CARBONATE 6 [hp_X]/1 mL; LYCOPODIUM CLAVATUM SPORE 6 [hp_X]/1 mL; SUCROSE 6 [hp_X]/1 mL; THYROID, BOVINE 6 [hp_X]/1 mL; SUS SCROFA HYPOTHALAMUS 8 [hp_X]/1 mL; ARISTOLOCHIA CLEMATITIS ROOT 9 [hp_X]/1 mL; ESTRONE 10 [hp_X]/1 mL; GOLD MONOSULFIDE 12 [hp_X]/1 mL; CANDIDA ALBICANS 12 [hp_X]/1 mL; ANAMIRTA COCCULUS SEED 12 [hp_X]/1 mL; CONIUM MACULATUM FLOWERING TOP 12 [hp_X]/1 mL; CYCLAMEN PURPURASCENS TUBER 12 [hp_X]/1 mL; MICRURUS CORALLINUS VENOM 12 [hp_X]/1 mL; CANIS LUPUS FAMILIARIS MILK 12 [hp_X]/1 mL; LACHESIS MUTA VENOM 12 [hp_X]/1 mL; MAGNESIUM CARBONATE 12 [hp_X]/1 mL; PULSATILLA PRATENSIS WHOLE 12 [hp_X]/1 mL; TIN 12 [hp_X]/1 mL
INACTIVE INGREDIENTS: WATER; ALCOHOL

DRUG FACTS:

ACTIVE INGREDIENTS:

Agnus Castus 6X, Cimicifuga Racemosa 6X, Kali Carbonicum 6X, Lycopodium Clavatum 6X, Saccharum Officinale 6X, Thyroidinum (Bovine) 6X, 12X, 30X, Hypothalamus Suis 8X, Aristolochia Clematitis 9X, Folliculinum 10X, 12X, 30X, Aurum Sulphuratum 12X, Candida Albicans 12X, 30X, Cocculus Indicus 12X, Conium Maculatum 12X, Cyclamen Europaeum 12X, Elaps Corallinus 12X, Lac Caninum 12X, Lachesis Mutus 12X, Magnesia Carbonica 12X, Pulsatilla (Pratensis) 12X, Stannum Metallicum 12X.

HOMEOPATHIC INDICATIONS:

For the temporary relief of symptoms related to premenstrual syndrome, such as mood swings, irritability, anger, sadness, weeping, anxiety, acne, bowel congestion, head pain, muscle pain before menses.**

**These statements are based upon homeopathic principles. They have not been reviewed by the Food and Drug Administration.

WARNINGS:

Keep out of reach of children. In case of overdose, contact physician or Poison Control Center right away.

If pregnant or breast-feeding, ask a health professional before use.

Tamper seal: "Sealed for Your Protection." Do not use if seal is broken or missing.

Keep out of reach of children. In case of overdose, contact physician or Poison Control Center right away.

DIRECTIONS:

1-10 drops under the tongue, 3 times a day or as directed by a health professional. Consult a physician for use in children under 12 years of age.

HOMEOPATHIC INDICATIONS:

For the temporary relief of symptoms related to premenstrual syndrome, such as mood swings, irritability, anger, sadness, weeping, anxiety, acne, bowel congestion, head pain, muscle pain before menses.**

**These statements are based upon homeopathic principles. They have not been reviewed by the Food and Drug Administration.

INACTIVE INGREDIENTS:

Demineralized Water, 25% Ethanol

QUESTIONS:

Dist. By: Deseret Biologicals, Inc.

469 W. Parkland Drive

Sandy, UT 84070 www.desbio.com

PACKAGE LABEL DISPLAY:

DESBIO

NDC 43742-1342-1

HOMEOPATHIC

PMS

RELIEF

1 FL OZ (30 ml)